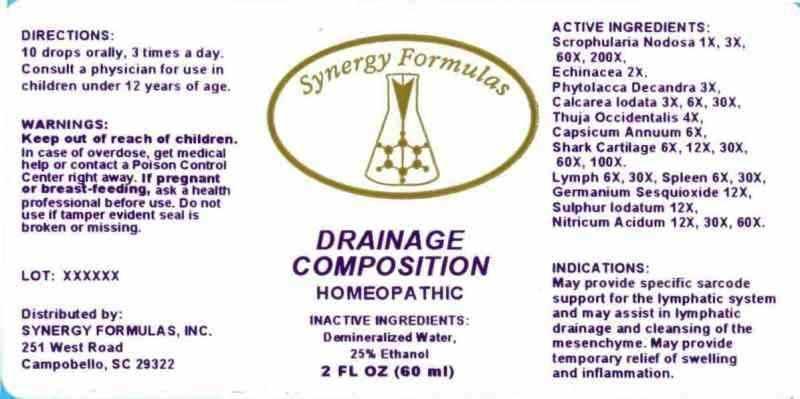 DRUG LABEL: Drainage Composition
NDC: 43772-0024 | Form: LIQUID
Manufacturer: Synergy Formulas, Inc.
Category: homeopathic | Type: HUMAN OTC DRUG LABEL
Date: 20140110

ACTIVE INGREDIENTS: SHARK CARTILAGE 6 [hp_X]/1 mL; SCROPHULARIA NODOSA 1 [hp_X]/1 mL; ECHINACEA, UNSPECIFIED 2 [hp_X]/1 mL; PHYTOLACCA AMERICANA ROOT 3 [hp_X]/1 mL; GERMANIUM SESQUIOXIDE 12 [hp_X]/1 mL; CALCIUM IODIDE 3 [hp_X]/1 mL; SUS SCROFA LYMPH 6 [hp_X]/1 mL; SUS SCROFA SPLEEN 6 [hp_X]/1 mL; THUJA OCCIDENTALIS LEAF 4 [hp_X]/1 mL; CAPSICUM 6 [hp_X]/1 mL; SULFUR IODIDE 12 [hp_X]/1 mL; NITRIC ACID 12 [hp_X]/1 mL
INACTIVE INGREDIENTS: WATER; ALCOHOL

DRUG FACTS:

ACTIVE INGREDIENTS:

Shark Cartilage 6X, 12X, 30X, 60X, 100X, Scrophularia Nodosa 1X, 3X, 60X, 200X, Echinacea 2X, Phytolacca Decandra 3X, Germanium Sesquioxide 12X, Calcarea Iodata 3X, 6X, 30X, Lymph (Suis) 6X, 30X, Spleen (Suis) 6X, 30X, Thuja Occidentalis 4X, Capsicum Annuum 6X, Sulphur Iodatum 12X, Nitricum Acidum 12X, 30X, 60X

INDICATIONS:

May provide specific sarcode support for the lymphatic system and may assist in lymphatic drainage and cleansing of the mesenchyme. May provide temporary relief of swelling and inflammation.

WARNINGS:

Keep out of reach of children. In case of overdose, get medical help or contact a Poison Control Center right away.

If pregnant or breast-feeding, ask a health professional before use.

Do not use if tamper evident seal is broken or missing.

Keep out of reach of children. In case of overdose, get medical help or contact a Poison Control Center right away.

DIRECTIONS:

10 drops orally, 3 times a day. Consult a physician for use in children under 12 years of age.

INDICATIONS:

May provide specific sarcode support for the lymphatic system and may assist in lymphatic drainage and cleansing of the mesenchyme. May provide temporary relief of swelling and inflammation.

INACTIVE INGREDIENTS:

Demineralized Water, 25% Ethanol

QUESTIONS:

Distributed by:

SYNERGY FORMULAS, INC.

251 West Road

Campobello, SC 29322

PACKAGE DISPLAY LABEL:

Synergy Formulas

Drainage Composition

HOMEOPATHIC

2 FL OZ (60 ml)